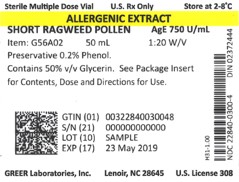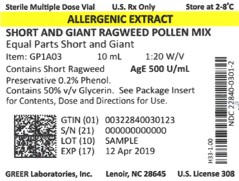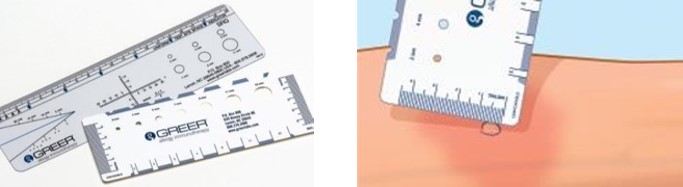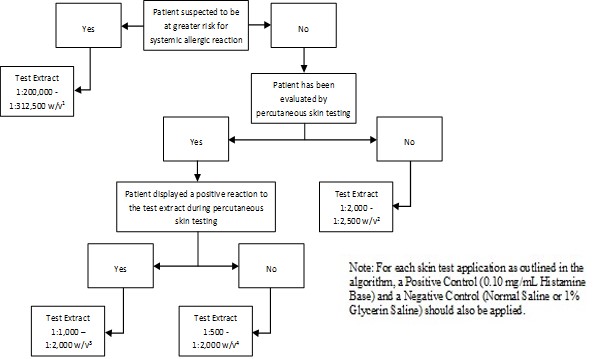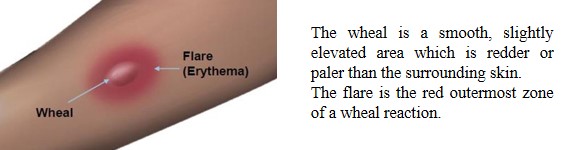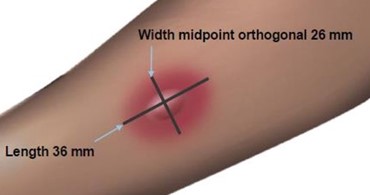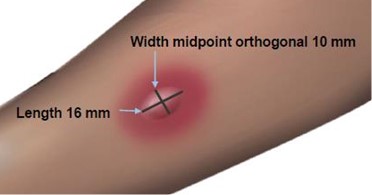 DRUG LABEL: Short and Giant Ragweed Pollen Mix
NDC: 22840-0301 | Form: SOLUTION
Manufacturer: Greer Laboratories, Inc.
Category: other | Type: NON-STANDARDIZED ALLERGENIC LABEL
Date: 20250603

ACTIVE INGREDIENTS: AMBROSIA ARTEMISIIFOLIA POLLEN 0.025 g/1 mL; AMBROSIA TRIFIDA POLLEN 0.025 g/1 mL
INACTIVE INGREDIENTS: SODIUM BICARBONATE; PHENOL; SODIUM CHLORIDE; GLYCERIN

ALLERGENIC EXTRACTS
Short Ragweed Pollen and Short and Giant Ragweed Pollen Mix

HIGHLIGHTS OF PRESCRIBING INFORMATION

These highlights do not include all the information needed to use Short Ragweed Pollen Allergenic Extract and Short and Giant Ragweed Pollen Mix Allergenic Extract safely and effectively. See full prescribing information for Short Ragweed Pollen Allergenic Extract and Short and Giant Ragweed Pollen Mix Allergenic Extract.

Short Ragweed Pollen Allergenic Extract

Short and Giant Ragweed Pollen Mix Allergenic Extract

Solutions for percutaneous, intradermal, or subcutaneous administration.

Initial U.S. Approval: 1982

WARNING: SEVERE ALLERGIC REACTIONS

See full prescribing information for complete boxed warning.

- Short Ragweed Pollen Allergenic Extract and Short and Giant Ragweed Pollen Mix Allergenic Extract can cause severe life-threatening systemic reactions, including anaphylaxis. (5.1)
- Do not administer these products to patients with severe, unstable or uncontrolled asthma. (4)
- Observe patients in the office for at least 30 minutes following treatment.Emergency measures and personnel trained in their use must be available immediately in the event of a life-threatening reaction. (5.1)
- Patients with extreme sensitivity to these products, on an accelerated immunotherapy build-up, switching to another lot, receiving high doses of these products, or those also exposed to similar allergens may be at increased risk of a severe allergic reaction. (5.1)
- These products may not be suitable for patients with certain underlying medical conditions that may reduce their ability to survive a serious allergic reaction, or for patients who may be unresponsive to epinephrine or inhaled bronchodilators, such as those taking beta-blockers. (5.1, 5.2)

INDICATIONS AND USAGE

Short Ragweed Pollen Allergenic Extract and Short and Giant Ragweed Pollen Mix Allergenic Extract are indicated for:

- Skin test diagnosis of patients with a clinical history of allergy to ragweed pollen (Short Ragweed or Short and Giant Ragweed pollen). (1)
- Immunotherapy for the reduction of ragweed pollen-induced allergic symptoms confirmed by positive skin test or by in vitro testing for pollen-specific IgE antibodies for Short and/or Giant Ragweed pollen. (1)

DOSAGE AND ADMINISTRATION

For percutaneous, intradermal or subcutaneous use only.

The extracts are diluted with sterile diluents when used for intradermal testing or subcutaneous immunotherapy. For percutaneous testing, the extracts are diluted with sterile diluents in patients expected to be at greater risk for systemic allergic reaction. Dosages vary by mode of administration and by individual response. See full prescribing information for instructions on preparation, administration, and adjustments of dose. (2.1)

DOSAGE FORMS AND STRENGTHS

Short Ragweed Pollen Allergenic Extract solution; stock concentrates at 1:20 weight/volume with Antigen E (Amb a 1) concentration labeled in Units/milliliter. (3)

Short and Giant Ragweed Pollen Mix Allergenic Extract solution: stock concentrates at 1:20 weight/volume with Antigen E (Amb a 1) concentration labeled in Units/milliliter. (3)

CONTRAINDICATIONS

- Severe, unstable or uncontrolled asthma. (4)
- History of any severe systemic allergic reaction or any severe local reaction to subcutaneous allergen immunotherapy. (4)

WARNINGS AND PRECAUTIONS

Severe allergic reactions have occurred following the administration of other allergenic extracts and may occur in individuals following the administration of Short Ragweed Pollen Allergenic Extract or Short and Giant Ragweed Pollen Mix Allergenic Extract in the following situations:

- Extreme sensitivity to these products, receipt of high doses of these products, or concomitant exposure to similar environmental allergens. (5.1)
- Receiving an accelerated immunotherapy build-up schedule (e.g., “rush” immunotherapy), or changing from one allergenic lot to another. (5.1)

ADVERSE REACTIONS

The most common adverse reactions occurring in 26 to 82% of all patients who receive subcutaneous immunotherapy are local adverse reactions at the injection site (e.g., erythema, itching, swelling, tenderness, pain). (6)

Systemic adverse reactions, occurring in < 7% of patients who receive subcutaneous immunotherapy, include generalized skin erythema, urticaria, pruritus, angioedema, rhinitis, wheezing, laryngeal edema, and hypotension. These can be fatal. (6)

To report SUSPECTED ADVERSE REACTIONS, contact GREER Laboratories, Inc. at 1-855-274-1322 or FDA at 1-800-FDA-1088 or www.fda.gov/medwatch.

DRUG INTERACTIONS

Antihistamines and other medications that suppress histamine, including topical corticosteroids, topical anesthetics and tricyclic antidepressants can interfere with skin test results. (7.1)

See 17 for PATIENT COUNSELING INFORMATION

FULL PRESCRIBING INFORMATION

WARNING: SEVERE ALLERGIC REACTIONS

- Short Ragweed Pollen Allergenic Extract and Short and Giant Ragweed Pollen Mix Allergenic Extract can cause severe life-threatening systemic reactions, including anaphylaxis. (5.1)
- Do not administer these products to patients with severe, unstable or uncontrolled asthma. (4)
- Observe patients in the office for at least 30 minutes following treatment.Emergency measures and personnel trained in their use must be available immediately in the event of a life-threatening reaction. (5.1)
- Patients with extreme sensitivity to these products, those on an accelerated immunotherapy build-up schedule, those switching to another allergenic lot, those receiving high doses of these products, or those also exposed to similar allergens may be at increased risk of a severe allergic reaction. (5.1)
- These products may not be suitable for patients with certain underlying medical conditions that may reduce their ability to survive a serious allergic reaction. (5.1)
- These products may not be suitable for patients who may be unresponsive to epinephrine or inhaled bronchodilators, such as those taking beta-blockers. (5.2)

1 INDICATIONS AND USAGE

Short Ragweed Pollen Allergenic Extract and Short and Giant Ragweed Pollen Mix Allergenic Extract are indicated for:

- Skin test diagnosis of patients with a clinical history of allergy to ragweed pollen (Short Ragweed or Short and Giant Ragweed Pollen).
- Immunotherapy for the reduction of ragweed pollen-induced allergic symptoms confirmed by positive skin test or by in vitro testing for pollen-specific IgE antibodies for Short and/or Giant Ragweed pollen.

2 DOSAGE AND ADMINISTRATION

For percutaneous, intradermal or subcutaneous use only.

The extracts are diluted with sterile diluents when used for intradermal testing or subcutaneous immunotherapy. For percutaneous testing, the extracts are diluted with sterile diluents in patients expected to be at greater risk for systemic allergic reaction. Dosages vary by mode of administration and by individual response.

2.1 Preparation for Administration

Parenteral drug products should be inspected visually for particulate matter and discoloration prior to administration, whenever solution and container permit. Discard solution if either of these conditions exist.

The extracts are diluted with sterile diluents when used for percutaneous and intradermal testing, or for subcutaneous immunotherapy.

Undiluted 1:20 weight/volume stock concentrate is used for percutaneous testing. To prepare 10-fold dilutions for percutaneous testing in patients suspected to be at greater risk for systemic allergic reaction, start with a 1:20 weight/volume stock concentrate. Proceed as in Table 1. The 10-fold dilution series uses 0.5 milliliters of concentrate added to 4.5 milliliters of sterile 50% glycerin diluent. Subsequent dilutions are made in a similar manner.

To prepare 10-fold dilutions for intradermal testing and immunotherapy, start with a 1:20 weight/volume stock concentrate. Proceed as in Table 1. The 10-fold dilution series uses 0.5 milliliter of concentrate added to 4.5 milliliters of sterile diluent (glycerin-free diluents for intradermal testing, glycerin-free or 10% glycerin saline diluents for immunotherapy). Subsequent dilutions are made in a similar manner.

Table 1: 10-fold Dilution Series
Dilution | Extract | Milliliters of Diluent | Dilution Strength | Dilution Strength [AgE (Amb a 1) Units/mL]
Dilution | Extract | Milliliters of Diluent | Dilution Strength | Short Ragweed Pollen | Short and Giant Ragweed Pollen Mix
0 | Concentrate |  | 1:20 | 150 - 300 | 75 - 150
1 | 0.5 mL Concentrate | 4.5 | 1:200 | 15 - 30 | 7.5 - 15
2 | 0.5 mL Dilution 1 | 4.5 | 1:2,000 | 1.5 - 3 | 0.75 - 1.5
3 | 0.5 mL Dilution 2 | 4.5 | 1:20,000 | 0.15 - 0.3 | 0.075 - 0.15
4 | 0.5 mL Dilution 3 | 4.5 | 1:200,000 | 0.015 - 0.03 | 0.0075 - 0.015
5 | 0.5 mL Dilution 4 | 4.5 | 1:2,000,000 | 0.0015 - 0.003 | 0.00075 - 0.0015
6 | 0.5 mL Dilution 5 | 4.5 | 1:20,000,000 | 0.00015 - 0.0003 | 0.000075 - 0.00015

Undiluted 1:20 weight/volume stock concentrate is typically used for percutaneous testing. To prepare 5-fold dilutions for percutaneous testing in patients suspected to be at greater risk for systemic allergic reaction, start with a 1:20 weight/volume stock concentrate. Proceed as in Table 2. The 5-fold dilution series uses 1 milliliter of concentrate added to 4 milliliters of sterile 50% glycerin diluent. Subsequent dilutions are made in a similar manner.

To prepare 5-fold dilutions for intradermal testing or immunotherapy, start with a 1:20 weight/volume (w/v) stock concentrate. Proceed as in Table 2. The 5-fold dilution series uses 1 milliliter of concentrate added to 4 milliliters of sterile diluent (glycerin-free diluents for intradermal testing, glycerin-free or 10% glycerin saline diluents for immunotherapy). Subsequent dilutions are made in a similar manner.

Table 2: 5-fold Dilution Series
Dilution | Extract | Milliliters of Diluent | Dilution Strength (w/v) | Dilution Strength [AgE (Amb a 1) Units/mL]
Dilution | Extract | Milliliters of Diluent | Dilution Strength (w/v) | Short Ragweed Pollen | Short and Giant Ragweed Pollen Mix
0 | Concentrate |  | 1:20 | 150 - 300 | 75 - 150
1 | 1 mL Concentrate | 4 | 1:100 | 30 - 60 | 15 - 30
2 | 1 mL Dilution 1 | 4 | 1:500 | 6 - 12 | 3 - 6
3 | 1 mL Dilution 2 | 4 | 1:2,500 | 1.2 - 2.4 | 0.06 - 1.2
4 | 1 mL Dilution 3 | 4 | 1:12,500 | 0.24 - 0.48 | 0.12 - 0.24
5 | 1 mL Dilution 5 | 4 | 1:62,500 | 0.048 - 0.096 | 0.024 - 0.048
6 | 1 mL Dilution 4 | 4 | 1:312,500 | 0.0096 - 0.0192 | 0.0048 - 0.0096

2.2 Diagnostic Testing

Diagnostic testing can be performed via percutaneous or intradermal administration of the Short Ragweed Pollen Allergenic Extract and Short and Giant Ragweed Pollen Mix Allergenic Extract. A positive skin test reaction must be interpreted in relation to the patient’s history and known exposure to the allergen.

If a skin test with the Short and Giant Ragweed Pollen Mix Allergenic Extract elicits a positive reaction, then the single-species ragweed pollen allergenic extracts can be used to determine the degree of sensitivity to each, and to guide in the selection of extracts and their concentration for immunotherapy, if indicated.

Percutaneous Skin Testing

Determine the patient’s sensitivity to the ragweed pollen allergens.

Prick or puncture testing: use 1:20 weight/volume extract stock concentrate.

In patients suspected to be at greater risk for systemic allergic reaction, initiate testing with serial 10-fold or 5-fold dilutions.

Preparation and Dose

For percutaneous testing (prick or puncture) use 1:20 weight/volume stock concentrate. If a lower concentration is desired in patients suspected to be at greater risk for a systemic allergic reaction, 10-fold or 5-fold dilutions of the concentrate can be tested.

Prick test: Place one drop of extract or control on the skin and, with a skin test device, pierce through the drop into the skin with a slight lifting motion. Alternatively, use skin test devices loaded with the extract from the storage trays in a similar manner, or in accordance with the device manufacturer’s recommendations.

Puncture test: Place one drop of extract or control on the skin and pierce the skin through the drop with a skin test device perpendicular to the skin. Alternatively, use skin test devices loaded with the extract from the storage trays in a similar manner, or in accordance with the device manufacturer’s recommendations.

Interpreting Results

When using percutaneous skin test devices, follow the directions provided with the test devices. A glycerinated histamine control solution (6 milligrams/milliliter or 1 milligram/milliliter histamine base) may be used as the positive control. A 50% glycerin saline solution may be used as the negative control.

Read and record skin test responses 15 to 20 minutes after exposure. Individual patient reactivity can vary with time, allergen potency, and/or immunotherapy, as well as testing technique. The most reliable method of recording a skin test reaction is to measure the largest diameter of both wheal and erythema. While some correlation exists between the size of the skin test reaction and the degree of sensitivity, other factors should be considered in the diagnosis of allergy to specific allergens (see Figure 1 below).

Figure 1: Measurement of Wheal and Flare

To measure the Wheal and Flare, use a paper or plastic millimeter skin reaction guide as shown below.

When the timer goes off 15 minutes after application of the skin test, measure the length and midpoint orthogonal width of each flare and wheal from the inner edge of the reaction.

The length of the skin test is defined as the largest diameter and the width of the skin test is defined as the diameter perpendicular to the length at its midpoint. Consider the wheal and flare as separate entities. First measure the flare and then independently measure the wheal.

Measuring the Flare

Measuring the Wheal

The average diameter measurement in the example above of the flare is (26 mm + 36 mm)/2 = 31 mm and the average diameter of the wheal is (10 mm + 16 mm)/2 = 13 mm.

Responses to positive controls should be at least 3 millimeters larger than responses to the negative controls.

Negative controls should elicit no reaction or only reactions of small diameter (wheal less than 3 millimeters, erythema less than 5 millimeters).

If either the positive or negative control response does not meet the above criteria, results for allergenic extracts tested at the same time should be considered invalid and be repeated.

Intradermal Skin Testing

Preparation and Dose

For intradermal testing, use 1:20 weight/volume of Short Ragweed Pollen Allergenic Extract and Short and Giant Ragweed Pollen Mix Allergenic Extract stock concentrate solution. Dilute the stock concentrate solution with sterile diluent [see Dosage and Administration (2.1)]. Use normal or buffered saline or normal saline with human serum albumin (HSA) diluent. If the result from the initial test dose is negative, subsequent intradermal tests using increasingly stronger doses may be performed up to the maximum recommended strength of 1:25 volume to volume dilution of the extract concentrate solution.

Inject 0.02 milliliters of the following solutions intradermally as shown in Figure 2:

Figure 2: Algorithm for Dilution of Stock Concentrate Solution of Short Ragweed Pollen Allergenic Extract and Short and Giant Ragweed Pollen Mix Allergenic Extract for Intradermal Skin Testing

^1 Corresponds to 1:10,000 - 1:15,625 volume to volume dilution of extract concentrate solution

^2 Corresponds to 1:100 - 1:125 volume to volume dilution of extract concentrate solution

^3 Corresponds to 1:50 - 1:100 volume to volume dilution of extract concentrate solution

^4 Corresponds to 1:25 - 1:100 volume to volume dilution of extract concentrate solution

2.3 Immunotherapy

For subcutaneous administration only.

Preparation and Dose

Stock concentrates of Short Ragweed Pollen Allergenic Extract and Short and Giant Ragweed Pollen Mix Allergenic Extract are available at 1:20 weight/volume in 50% glycerin saline for immunotherapy. Stock concentrates are diluted in normal saline, buffered saline, HSA saline, or 10% glycerin saline, depending on the patient’s reactivity to the diluent. See Table 1 and Table 2 for dilution preparation.

Administration of Immunotherapy

Administer immunotherapy by subcutaneous injection in the lateral aspect of the upper arm or thigh. Avoid injection directly into any blood vessel.

The optimal interval between doses of allergenic extract varies among individuals. Injections are usually given 1 to 2 times per week until the maintenance dose is reached, at which time the injection interval is increased to 2, then 3, and finally 4 weeks. Dosages vary by mode of administration, and by clinical response and tolerance. The minimum course of treatment may be three to five years, depending on the clinical response.

Guidelines for Immunotherapy

The initial dose of the extract should be based on the skin test reactivity. In patients suspected to be at greater risk for systemic allergic reaction by history and skin test, the initial dose of the extract should be 0.05 milliliter of a 1:20,000,000 to 1:2,000,000 weight/volume extract dilution. Patients not suspected to be at greater risk for systemic allergic reaction may be started at a 0.1 milliliter of a 1:200,000 to 1:20,000 weight/volume extract dilution.

The dose of allergenic extract is increased at each injection by no more than 50% of the previous dose, and the next increment is governed by the response to the last injection.

Select the maximum tolerated maintenance dose based on the patient's clinical response and tolerance. Doses larger than 0.2 milliliter of the stock concentrate are rarely administered because an extract mixed in 50% glycerin diluent can cause discomfort upon injection.

Dosage Modification Guidelines for Immunotherapy

The following conditions may indicate a need to withhold or reduce the dosage of immunotherapy.

- Symptoms of rhinitis and/or asthma
- Infection accompanied by fever
- Exposure to excessive amounts of clinically relevant environmental allergen prior to a scheduled injection
- Large local reactions that persist for longer than 24 hours can be an indication for repeating the previous dose or reducing the dose at the next administration

Any evidence of a systemic adverse reaction is an indication for a significant reduction (at least 75%) in the subsequent dose. Repeated systemic adverse reactions are sufficient reason for the cessation of further attempts to increase the dose.

Local adverse reactions require a decrease in the next dose by at least 50%. Proceed cautiously in subsequent dosing. In situations prompting dose reduction, once the reduced dose is tolerated, a cautious increase in dosage can be attempted.

Changing extract to a different lot or from a different manufacturer: When switching patients to a different lot of extract, or from another manufacturer’s extract, decrease the starting dose. Because manufacturing processes and sources of raw materials differ among manufacturers, the interchangeability of extracts from different manufacturers cannot be assured. In general, a dose reduction of 50 to 75% of the previous dose should be adequate, but each situation must be evaluated separately, considering the patient’s history of sensitivity, tolerance of previous injections, and other factors. Dose intervals should not exceed one week when rebuilding the dose.

Unscheduled gaps between treatments: Patients can lose tolerance for allergen injections during prolonged periods between doses, thus increasing their risk for an adverse reaction. The duration of tolerance between injections varies from patient to patient.

During the build-up phase, when patients receive injections 1 to 2 times per week, repeat or reduce the extract dosage if there has been a substantial time interval between injections. This depends on: 1) the concentration of allergen immunotherapy extract that is to be administered; 2) a previous history of systemic reactions; and 3) the degree of variation from the prescribed interval of time, with longer intervals since the last injection leading to greater reductions in the dose to be administered.

This suggested approach to dose modification, due to unscheduled gaps between treatments during the build-up phase, is not based on published evidence. The individual physician should use this or a similar protocol for the specific clinical setting.

Similarly, if unscheduled gaps occur during maintenance therapy, it may be necessary to reduce the dosage and bring the patient up to maintenance dosing using an established build-up protocol.

Changing from non-stabilized to human serum albumin (HSA) stabilized diluents: Allergenic extracts prepared with diluents containing HSA and 0.4% phenol are more stable than those prepared with diluents that do not contain stabilizers. When switching from a non-stabilized to an HSA‑stabilized diluent, consider lowering the dose for immunotherapy.

3 DOSAGE FORMS AND STRENGTHS

Short Ragweed Pollen Allergenic Extract solution: stock concentrate at 1:20 weight/volume with Antigen E (Amb a 1) concentration labeled in Units/milliliter.

Short and Giant Ragweed Pollen Mix Allergenic Extract solution: stock concentrate at 1:20 weight/volume with Antigen E (Amb a 1) concentration labeled in Units/milliliter.

4 CONTRAINDICATIONS

Short Ragweed Pollen Allergenic Extract and Short and Giant Ragweed Pollen Mix Allergenic Extract are contraindicated in patients with:

- Severe, unstable or uncontrolled asthma
- History of any severe systemic allergic reaction or any severe local reaction to subcutaneous allergen immunotherapy

5 WARNINGS AND PRECAUTIONS

5.1 Serious Systemic Adverse Reactions

Serious systemic adverse reactions have occurred following the administration of other allergenic extracts and may occur in individuals following the administration of Short Ragweed Pollen Allergenic Extract and Short and Giant Ragweed Pollen Mix Allergenic Extract in the following situations:

- Extreme sensitivity to ragweed pollen allergenic extracts
- Receipt of an accelerated immunotherapy build-up schedule (e.g., “rush” immunotherapy)
- Receipt of high doses of ragweed pollen allergenic extracts or concomitant exposure to similar environmental allergens
- Change from one allergenic lot to another allergenic lot

High-risk patients have had fatal reactions. Consider using more dilute preparations in patients suspected to be at greater risk of systemic allergic reaction [see Dosage and Administration (2.1)].

Administer these products in a healthcare setting under the supervision of a physician prepared to manage a severe systemic or a severe local allergic reaction. Observe patients in the office for at least 30 minutes following administration.^1

5.2 Epinephrine

Short Ragweed Pollen Allergenic Extract and Short and Giant Ragweed Pollen Mix Allergenic Extract may not be suitable for patients with certain medical conditions that may reduce the ability to survive a serious allergic reaction or increase the risk of adverse reactions after epinephrine administration. Examples of these medical conditions include but are not limited to: markedly compromised lung function (either chronic or acute), unstable angina, recent myocardial infarction, significant arrhythmia, and uncontrolled hypertension.

These products may not be suitable for patients who are taking medications that can potentiate or inhibit the effect of epinephrine. These medications include:

Βeta-adrenergic blockers: Patients taking beta-adrenergic blockers may be unresponsive to the usual doses of epinephrine used to treat serious systemic reactions, including anaphylaxis. Specifically, beta-adrenergic blockers antagonize the cardiostimulating and bronchodilating effects of epinephrine.

Alpha-adrenergic blockers, ergot alkaloids: Patients taking alpha-adrenergic blockers may be unresponsive to the usual doses of epinephrine used to treat serious systemic reactions, including anaphylaxis. Specifically, alpha-adrenergic blockers antagonize the vasoconstricting and hypertensive effects of epinephrine. Similarly, ergot alkaloids may reverse the pressor effects of epinephrine.

Tricyclic antidepressants, levothyroxine sodium, monoamine oxidase inhibitors, and certain antihistamines: The adverse effects of epinephrine may be potentiated in patients taking tricyclic antidepressants, levothyroxine sodium, monoamine oxidase inhibitors, and the antihistamines chlorpheniramine, and diphenhydramine.

Cardiac glycosides, diuretics: Patients who receive epinephrine while taking cardiac glycosides or diuretics should be observed carefully for the development of cardiac arrhythmias.

5.3 Cross-Reactions and Dose Sensitivity

Since many ragweed species tend to cross-react, the total allergen content should be considered in determining the maximum maintenance dose of the mixture. The total allergen content in Short Ragweed Pollen Allergenic Extract and Short and Giant Ragweed Pollen Mix Allergenic Extract can be comparable to that of Short Ragweed Pollen Allergenic Extract at the same weight/volume strength.

Determine the initial dilution of allergenic extract, starting dose, and progression of dosage based on the patient’s history and results of skin tests [see Dosage and Administration (2.2)].^2 Strongly positive skin tests can be indicators for potential systemic adverse reactions.

6 ADVERSE REACTIONS

The most common adverse reactions, occurring in 26 to 82% of all patients who receive subcutaneous immunotherapy, are local adverse reactions at the injection site (e.g., erythema, itching, swelling, tenderness, pain).^1 Systemic adverse reactions, occurring in < 7% of patients who receive subcutaneous immunotherapy,^3,4 include generalized skin erythema, urticaria, pruritus, angioedema, rhinitis, wheezing, laryngeal edema, and hypotension. These can be fatal.^1

7 DRUG INTERACTIONS

7.1 Antihistamines

Do not perform skin testing with allergenic extracts within 3 to 10 days of use of first-generation H1-histamine receptor blockers (e.g., clemastine, diphenhydramine) and second-generation antihistamines (e.g., loratadine, cetirizine). These products suppress histamine skin test reactions and could mask a positive response.^2

7.2 Topical Corticosteroids and Topical Anesthetics

Topical corticosteroids can suppress skin reactivity; therefore, discontinue use at the skin test site for 2 to 3 weeks before skin testing. Avoid use of topical local anesthetics at skin test sites as they can suppress flare responses.^2

7.3 Tricyclic Antidepressants

Tricyclic antidepressants can have potent antihistamine effects that can affect skin testing. If tricyclic medication has been recently discontinued allow 7 to 14 days before initiating skin testing.^2

8 USE IN SPECIFIC POPULATIONS

8.1 Pregnancy

Risk Summary

All pregnancies have a risk of birth defect, loss, or other adverse outcomes. In the U.S. general population, the estimated background risk of major birth defects and miscarriage in clinically recognized pregnancies is 2 to 4% and 15 to 20%, respectively. There are no human or animal data to establish the presence or absence of Short Ragweed Pollen Allergenic Extract and Short and Giant Ragweed Pollen Mix Allergenic Extract Allergenic Extract-associated risks during pregnancy.

8.2 Lactation

Risk Summary

It is not known whether these productsError! Document Variable not defined. are present in human milk. Data are not available to assess the effects of these extracts on the breastfed child or on milk production/excretion. The developmental and health benefits of breastfeeding should be considered along with the mother’s clinical need for these products and any potential adverse effects on the breastfed child from the extracts or from the underlying maternal condition.

8.4 Pediatric Use

For use of these products in children younger than 5 years of age, consideration should be given to the patients’ ability to comply and cooperate with allergen immunotherapy and the potential for difficulty in communicating with the child regarding systemic reactions.^1

8.5 Geriatric Use

Data are not available to determine if subjects 65 years of age and older respond differently than younger subjects.

11 DESCRIPTION

Short Ragweed Pollen Allergenic Extract and Short and Giant Ragweed Pollen Mix Allergenic Extract are sterile solutions of extracted plant pollens. Each vial contains sterile ragweed extract (short ragweed pollen or short ragweed and giant ragweed pollen mixture) at 1:20 weight/volume, 50% glycerin volume/volume, and 0.2% phenol volume/volume (preservative). Inactive ingredients include 0.25% sodium chloride for isotonicity and 0.25% sodium bicarbonate as a buffer.

These products should be clear light yellow to brownish solutions that are free of particulate matter.

These products are standardized by comparison to reference standards supplied by the Center for Biologics Evaluation and Research (CBER) of the FDA, labeled in Antigen E (Amb a 1) Units/milliliter.^5,6,7,8 The Antigen E concentration of the 1:20 weight/volume extracts is determined by radial immunodiffusion using FDA short ragweed reference standards. The extracts are labeled in both Antigen E (AgE) Units/milliliter and weight/volume extraction ratio.

12 CLINICAL PHARMACOLOGY

12.1 Mechanism of Action

The skin test reaction results from interaction of the introduced allergen and allergen-specific IgE antibodies bound to mast cells, leading to mast cell degranulation and release of histamine, tryptase and other mediators, which results in the formation of the wheal and flare.

The precise mechanisms of action of allergen immunotherapy are not known. Immunologic responses to immunotherapy include changes in allergen-specific IgE levels, allergen-specific IgG levels, and regulatory T cell responses.^1

14 CLINICAL STUDIES

Studies with ragweed extracts and Antigen E immunotherapy have demonstrated significant symptom amelioration in ragweed-allergic individuals.^9,10

15 REFERENCES

1. Cox L, Nelson H, Lockey R. Allergen immunotherapy: a practice parameter third update. J Allergy Clin Immunol. 2011; 127(1):S1-S55.
2. Bernstein IL, Li JT, Bernstein DI, Hamilton R, Spector SL, Tan R, et al. Allergy diagnostic testing: an updated practice parameter. Ann Allergy Asthma Immunol. 2008; 100:S1-S148.
3. Greenberg MA, Kaufman CR, Gonzalez GE, et al. Late and immediate systemic-allergic reactions to inhalant allergen immunotherapy. J Allergy Clin Immunol. 1986;77:865-870.
4. Ragusa VF, Massolo A. Non-fatal systemic reactions to subcutaneous immunotherapy: a 20‑year experience comparison of two 10-year periods. Allerg Immunol (Paris) 2004;36:52‑55.
5. Turkeltaub PC, Rastogi SC, Baer H, et al. A standardized quantitative skin-test assay of allergen potency and stability: studies on the allergen dose-response curve and effect of wheal, erythema, and patient selection on assay results. J Allergy Clin Immunol. 1982; 70(5):343-352.
6. ELISA competition assay. Methods of the Allergenic Products Testing Laboratory. Rockville, MD: Laboratory of Immunobiochemistry, Division of Allergenic Products and Parasitology, Center for Biologics Evaluation and Research, Food and Drug Administration; October 1993. (On file)
7. Turkeltaub PC, Rastogi SC. Quantitative intradermal procedure for evaluation of subject sensitivity to standardized allergenic extracts and for assignment of bioequivalent allergy units to reference preparations using the ID50EAL method. Rockville, MD: Laboratory of Immunobiochemistry, Division of Allergenic Products and Parasitology, Center for Biologics Evaluation and Research, Food and Drug Administration; November 1994. (On file)
8. Turkeltaub PC. Assignment of bioequivalent allergy units based on biological standardization methods. Arbeiten aus dem Paul Ehrlich Institut (Bundesamt fur Sera und Impfstoffe), Band 52, Gustav Fischer Verlag, Stuttgart-New York, 1988; (82):19‑40.
9. Norman PS, Winkenwerder WL, Lichtenstein LM. Immunotherapy of hay fever with ragweed antigen E: comparisons with whole pollen extract and placebos. J Allergy. 1968; 42(2):93-108.
10. Arbesman CE, et al. Treatment of ragweed-sensitive patients with Antigen E and ragweed extract: Clinical and immunologic studies. J Allergy. 1967; 39(2):124.

16 HOW SUPPLIED/STORAGE AND HANDLING

16.1 How Supplied

Short Ragweed Pollen Allergenic Extract and Short and Giant Ragweed Pollen Mix Allergenic Extract are supplied as stock concentrate at 1:20 weight/volume in 50% glycerin for use in percutaneous skin testing, intradermal testing, and subcutaneous immunotherapy. These products are labeled in AgE Units/milliliter and are provided in 5, 10, and 50 milliliter vials.

These products are supplied as follows:

Short Ragweed Pollen Allergenic Extract
NDC Number | Strength/Containier
22840-0300-5 | 1:20 w/v, 5 mL dropper vial for prick (skin) testing
22840-0300-2 | 1:20 w/v, 10 mL multi-dose vial
22840-0300-4 | 1:20 w/v, 50 mL multi-dose vial
Short and Giant Ragweed Pollen Mix Allergenic Extract
NDC Number | Strength/Container
22840-0301-5 | 1:20 w/v, 5 mL dropper vial for prick (skin) testing
22840-0301-2 | 1:20 w/v, 10 mL multi-dose vial
22840-0301-4 | 1:20 w/v, 50 mL multi-dose vial

16.2 Storage and Handling

Maintain at 2 to 8°C (36 to 46°F) during storage and use.

Dilutions of concentrated extract result in a glycerin content of less than 50%, which can result in reduced stability. Extract dilutions at 1:100 v/v of the 1:20 weight/volume concentrate should be kept no longer than a month, and more dilute solutions no more than a week. The potency of a dilution can be checked by skin test comparison to a fresh dilution of the extract on a known ragweed-allergic patient.

17 PATIENT COUNSELING INFORMATION

Instruct patient to remain under observation in the office for 30 minutes or longer after an injection.

Caution patient that reactions can occur more than 30 minutes after skin testing or an injection.

Instruct patient to recognize the following symptoms as adverse reactions and to immediately return to the office or immediately seek other medical attention if any of these symptoms occur following skin testing or an injection:

- Unusual swelling and/or tenderness at the injection site
- Hives or itching of the skin
- Swelling of face and/or mouth
- Sneezing, coughing or wheezing
- Shortness of breath
- Nausea
- Dizziness or faintness

Manufacturer:

U.S. License No. 308
Greer Laboratories, Inc.
Lenoir, NC 28645 U.S.A